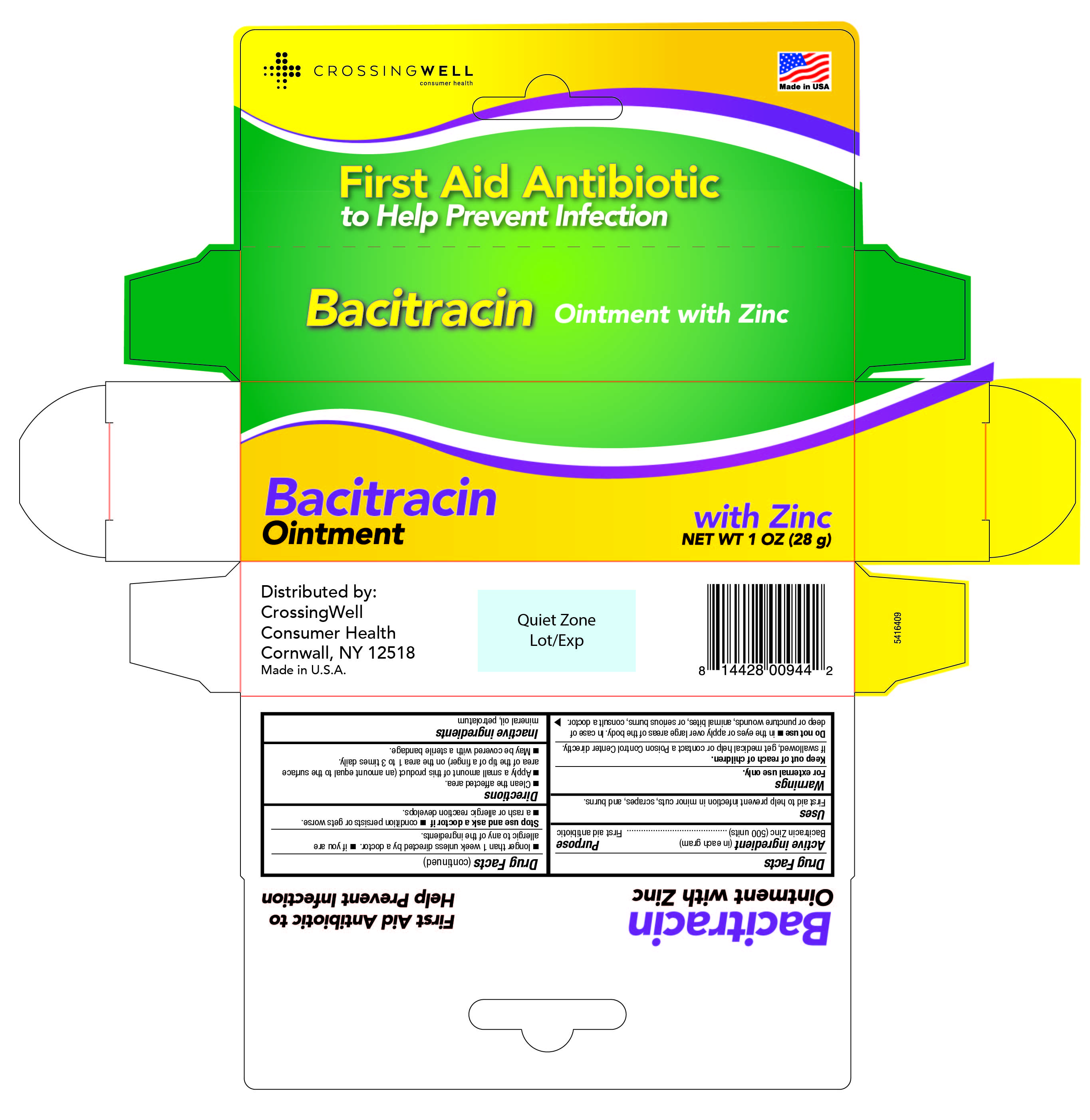 DRUG LABEL: Single Antibiotic with Bacitracin
NDC: 52412-750 | Form: OINTMENT
Manufacturer: Randob Labs Ltd.
Category: otc | Type: HUMAN OTC DRUG LABEL
Date: 20241230

ACTIVE INGREDIENTS: BACITRACIN ZINC 400 [USP'U]/1 g
INACTIVE INGREDIENTS: PETROLATUM

Single antibiotic with Bacitracin

Drug Facts

Active Ingredient (in each gram)

Bacitracin zinc (500 units bacitracin)

Purpose

First Aid Antibiotic

Uses:

First aid to help prevent infection in minor cuts, scrapes, and burns.

Warnings:

KEEP OUT OF REACH OF CHILDREN

For external use only. Keep out of reach of children.

If ingested, get medical help or contact a Poison Control Center directly.

Do Not Use:

- in the eyes or over large areas of the body, or on puncture wounds, animal bites or serious burns
- for more than 1 week unless directed by a doctor
- if allergic to any of the ingredients

Stop use, ask a doctor if:

- condition persists or gets worse
- a rash or allergic reaction develops

Directions:

- clean affected area
- apply a small amount of this product (equal to the surface area of the tip of finger) 1 to 3 times daily
- may cover with a sterile bandage

Inactive ingredients:

mineral oil, petrolatum

Questions or Comments?

1-800-456-7077

First Aid Antibiotic

NDC 52412-750-10

CrossingWell Consumer Health

Bacitracin Ointment with Zinc

First Aid Antibiotic to Help Prevent Infection

Net Wt 1oz (28g)